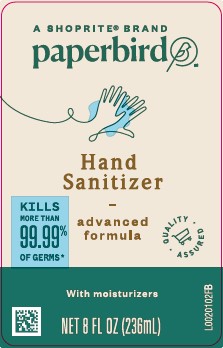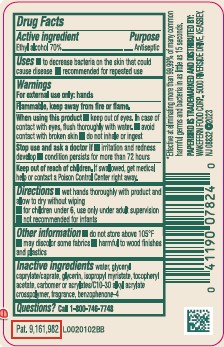 DRUG LABEL: Advanced Hand Sanitizer
NDC: 41190-370 | Form: GEL
Manufacturer: Wakefern Food Corp.
Category: otc | Type: HUMAN OTC DRUG LABEL
Date: 20260213

ACTIVE INGREDIENTS: ALCOHOL 70 mL/100 mL
INACTIVE INGREDIENTS: WATER; GLYCERYL CAPRYLATE/CAPRATE; GLYCERIN; ISOPROPYL MYRISTATE; .ALPHA.-TOCOPHEROL ACETATE; CARBOMER COPOLYMER TYPE B (ALLYL PENTAERYTHRITOL CROSSLINKED); SULISOBENZONE

Paperbird 370.001/370AE rev 1
Advanced Hand Sanitizer

Active Ingredient

Ethyl alcohol 70%

Purpose

Antiseptic

Uses

- to decrease bacteria on the skin that could cause disease
- recommended for repeated use

Warnings

For external use only: hands

Flammable, keep away from fire or flame.

When using this product

- keep out of eyes. In case of contact with eyes, flush thoroughly with water.
- avoid contact with broken skin
- do not inhale or ingest

Stop use and ask a doctor if

- irritation and redness develop
- condition persists for more than 72 hours

Keep out of reach of children.

If swallowed, get medical help or contact a Poison Control Center right away.

Directions

- wet hands thoroughly with product and allow to dry without wiping
- for children under 6, use only under adult supervision
- not recommended for infants

Other information

- do not store above 105⁰ F
- may discolor some fabrics
- harmful to wood finishes and plastics

Inactive ingredients

water, glyceryl caprylate/caprate, glycerin, isopropyl myristate, tocopheryl acetate, acrylates/C10-30 alkyl acrylate crosspolymer, fragrance, benzophenone-4

Questions?

Call 1-800-746-7748

Claim

*Effective at eliminating more than 99.99% of many common harmful germs and bacteria in as little as 15 seconds.

PAPERBIRD IS TRADEMARKED AND DISTRIBUTED BY:

WAKEFERN FOOD CORP., 5000 RIVERSIDE DRIVE, KEASBEY, NJ 08832

2023

principal display panel

A SHOPRITE®BRAND

paperbird™

Hand Sanitizer

advanced formula

QUALITY ASSURED

KILLS MORE THAN 99.99% OF GERMS*

With moisturizers

NET 8 FL OZ (236 mL)